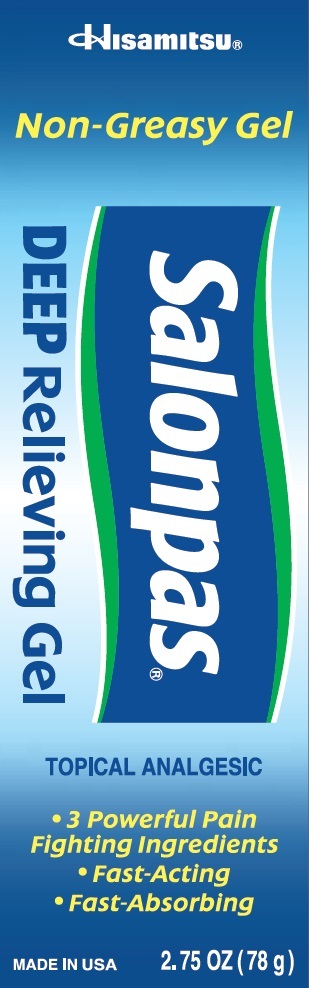 DRUG LABEL: Salonpas DEEP Relieving
NDC: 55328-900 | Form: GEL
Manufacturer: Hisamitsu America, Inc.
Category: otc | Type: HUMAN OTC DRUG LABEL
Date: 20241203

ACTIVE INGREDIENTS: CAMPHOR (SYNTHETIC) 3.10 g/100 g; MENTHOL 10.00 g/100 g; METHYL SALICYLATE 15.00 g/100 g
INACTIVE INGREDIENTS: AMMONIUM ACRYLOYLDIMETHYLTAURATE/VP COPOLYMER; DIMETHYL ISOSORBIDE; PROPYLENE GLYCOL; WATER

Active ingredients

Camphor 3.1%

Menthol 10.0%

Methyl salicylate 15.0%

Purpose

Topical analgesic

Uses

For temporary relief of minor aches and pains of muscles and joints associated with:

- simple backache
- sprains
- strains
- arthritis
- bruises

Warnings

For external use only

Allergy alert:

If prone to allergic reaction from aspirin or salicylates, consult a doctor before use.

Flammable:

Keep away from fire or flame.

Do not use

- on wounds or damaged skin
- with a heating pad
- if you are allergic to any ingredients of this product

When using this product

- use only as directed
- avoid contact with the eyes, mucous membranes or rashes
- do not bandage tightly

Stop use and ask a doctor if

- conditions worsen
- skin reactions such are redness, itching, rash, excessive irritation, burning sensation, swelling or blistering occur
- symptoms persist for more than 7 days
- symptoms clear up and occur again within a few days

If pregnant or breast-feeding,

ask a health professional before use.

Keep out of reach of children.

If swallowed, get medical help or contact a Poison Control Center right away.

Directions

Adults and children 12 years of age and over:

- clean and dry affected area
- apply a dime sized portion to the affected area
- massage thoroughly until absorbed into skin
- apply to affected area not more than 3 to 4 times daily

Children under 12 years of age: consult a doctor

Other information

- Avoid storing product in direct sunlight
- Protect product from excessive moisture
- Store at 20-25C (68-77F)
- Store with lid closed tightly

Inactive ingredients

ammonium acryloyldimethyltaurate/VP copolymer, dimethyl isosorbide, propylene glycol, SD alcohol 40-B, water

Questions or comments?

Toll free 1-800-826-8861

www.salonpas.us

Principal Display Panel

Hisamitsu

Non-Greasy Gel

Salonpas DEEP Relieving Gel

TOPICAL ANALGESIC

3 Powerful Pain Fighting Ingredients
Fast-Acting
Fast-Absorbing
MADE IN USA

2.75 OZ (78 g)